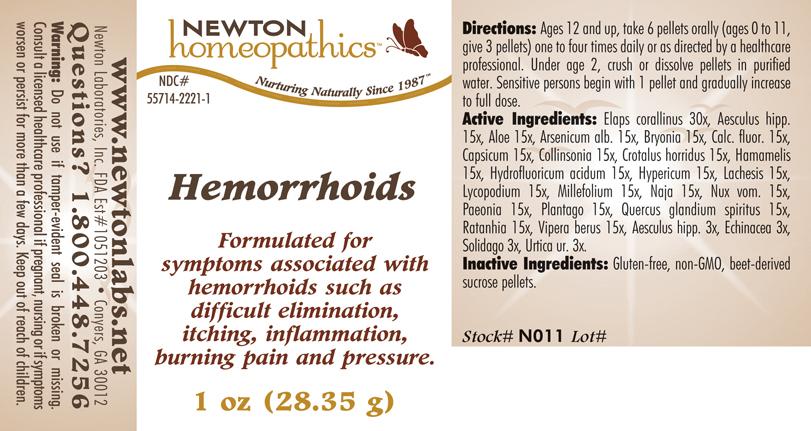 DRUG LABEL: Hemorrhoids 
NDC: 55714-2221 | Form: PELLET
Manufacturer: Newton Laboratories, Inc.
Category: homeopathic | Type: HUMAN OTC DRUG LABEL
Date: 20110301

ACTIVE INGREDIENTS: Micrurus Corallinus Venom 30 [hp_X]/1 g; Horse Chestnut 15 [hp_X]/1 g; Aloe 15 [hp_X]/1 g; Arsenic Trioxide 15 [hp_X]/1 g; Bryonia Alba Root 15 [hp_X]/1 g; Calcium Fluoride 15 [hp_X]/1 g; Capsicum 15 [hp_X]/1 g; Collinsonia Canadensis Root 15 [hp_X]/1 g; Crotalus Horridus Horridus Venom 15 [hp_X]/1 g; Hamamelis Virginiana Root Bark/stem Bark 15 [hp_X]/1 g; Hydrofluoric Acid 15 [hp_X]/1 g; Hypericum Perforatum 15 [hp_X]/1 g; Lachesis Muta Venom 15 [hp_X]/1 g; Lycopodium Clavatum Spore 15 [hp_X]/1 g; Achillea Millefolium 15 [hp_X]/1 g; Naja Naja Venom 15 [hp_X]/1 g; Strychnos Nux-vomica Seed 15 [hp_X]/1 g; Paeonia Officinalis Root 15 [hp_X]/1 g; Plantago Major 15 [hp_X]/1 g; Quercus Robur Nut 15 [hp_X]/1 g; Krameria Lappacea Root 15 [hp_X]/1 g; Vipera Berus Venom 15 [hp_X]/1 g; Echinacea, Unspecified 3 [hp_X]/1 g; Solidago Virgaurea Flowering Top 3 [hp_X]/1 g; Urtica Urens 3 [hp_X]/1 g
INACTIVE INGREDIENTS: Sucrose

Hemorrhoids

INDICATIONS & USAGE SECTION

Hemorrhoids Formulated for symptoms associated with hemorrhoids such as difficult elimination, itching, inflammation, burning pain and pressure.

DOSAGE & ADMINISTRATION SECTION

Directions: Ages 12 and up, take 6 pellets orally (ages 0 to 11, give 3 pellets) one to four times daily or as directed by a healthcare professional. Under age 2, crush or dissolve pellets in purified water. Sensitive persons begin with 1 pellet and gradually increase to full dose.

OTC - ACTIVE INGREDIENT SECTION

Elaps corallinus 30x, Aesculus hipp.15x, Aloe 15x, Arsenicum alb. 15x, Bryonia 15x, Calc. fluor. 15x, Capsicum 15x, Collinsonia 15x, Crotalus horridus 15x, Hamamelis 15x, Hydrofluoricum acidum 15x, Hypericum 15x, Lachesis 15x, Lycopodium 15x, Millefolium 15x, Naja 15x, Nux vom. 15x, Paeonia 15x, Plantago 15x, Quercus glandium spiritus 15x, Ratanhia 15x, Vipera berus 15x, Aesculus hipp. 3x, Echinacea 3x, Solidago 3x, Urtica ur. 3x.

OTC - PURPOSE SECTION

Formulated for symptoms associated with hemorrhoids such as difficult elimination, itching, inflammation, burning pain and pressure.

INACTIVE INGREDIENT SECTION

Inactive Ingredients: Gluten-free, non-GMO, beet-derived sucrose pellets.

QUESTIONS SECTION

www.newtonlabs.net Newton Laboratories, Inc. FDA Est # 1051203 - Conyers, GA 30012
Questions? 1.800.448.7256

WARNINGS SECTION

Warning: Do not use if tamper - evident seal is broken or missing. Consult a licensed healthcare professional if pregnant, nursing or if symptoms worsen or persist for more than a few days. Keep out of reach of children

OTC - PREGNANCY OR BREAST FEEDING SECTION

Consult a licensed healthcare professional if pregnant, nursing or if symptoms worsen or persist for more than a few days.

OTC - KEEP OUT OF REACH OF CHILDREN SECTION

Keep out of reach of children